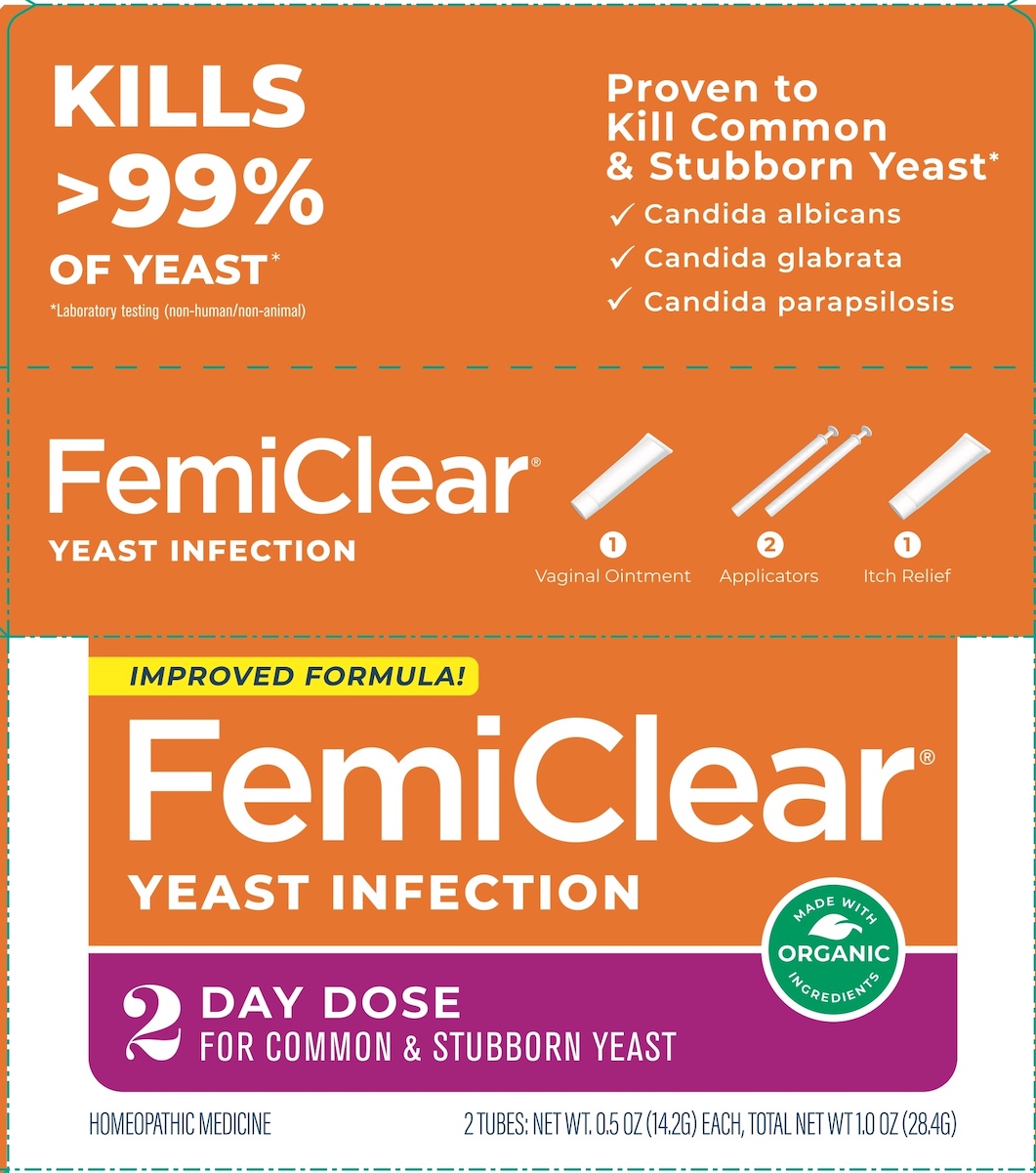 DRUG LABEL: FemiClear

NDC: 71042-011 | Form: KIT | Route: VAGINAL
Manufacturer: Organicare Nature's Science, LLC
Category: homeopathic | Type: HUMAN OTC DRUG LABEL
Date: 20251020

ACTIVE INGREDIENTS: CALENDULA OFFICINALIS FLOWERING TOP 3 [hp_X]/14 g; OLEUROPEIN 3 [hp_X]/14 g; MELALEUCA CAJUPUTI LEAF OIL 3 [hp_X]/14 g; OLEUROPEIN 3 [hp_X]/14 g; MATRICARIA CHAMOMILLA 3 [hp_X]/14 g
INACTIVE INGREDIENTS: OLIVE OIL; LAVENDER OIL; YELLOW WAX; LAVENDER OIL; OLIVE OIL; OATMEAL; YELLOW WAX

FEMICLEAR 2D YEAST INFECTION - IMPROVED FORMULA

Drug Facts

Active ingredients

Vaginal Ointment

Calendula 3X HPUS

Melaleuca 3X HPUS

Olive Extract (Oleuropein) 3X HPUS

Itch Relief

Chamomilla 3X HPUS

Olive Extract (Oleuropein) 3X HPUS

Purposes

Healing agent

Anti-yeast agent

Antimicrobial and healing agent

Anti-itch and inflammatory agent

Anti-microbial and healing agent

Uses

- treats vaginal yeast infections
- relieves external itching and irritation due to a vaginal yeast infection

Warnings

For vaginal use only.

Do not use if you have never had a vaginal yeast infection diagnosed by a doctor.

FemiClear may damage condoms and diaphragms and cause them to fail.

Ask a doctor before use if you have:

- vaginal itching and discomfort for the first time
- lower abdominal, back or shoulder pain, fever, chills, nausea, vomiting or foul-smelling vaginal discharge. You may have a more serious condition.
- vaginal yeast infections often (such as once a month or three in 6 months). You could be pregnant or have a serious underlying medical cause for your symptoms, including diabetes or a weakened immune system.
- been exposed to the human immunodeficiency virus (HIV) that causes AIDS

Do not use

- if you are allergic to any ingredient in this product

When using this product

- do not use tampons, douiches, spermicides, or other vaginal products. Condoms and diaphragms may be damaged and fail to prevent pregnancy or sexually transmitted infections (STIs)
- do not have vaginal intercourse
- mild increase in vaginal burning, itching, or irritation may occur
- if you do not get complete relief, ask a doctor before using another product

Stop use and ask a doctor if

- symptoms do not improve in 3 days
- symptoms remain after 7 days
- you get abdominal pain, fever, chills, vomiting, foul-smelling discharge, or hives

PREGNANCY OR BREAST FEEDING

If pregnant or breast-feeding, ask a health professional before use.

Keep out of reach of children. If swallowed, get medical help or contact a Poison Control Center right away.

Directions

- Adults and children 12 years or over:

Vaginal Ointment: use at bedtime, read enclosed instructions for complete directions.

- to protect clothes, use panty liner
- fill applicator with FemiClear Vaginal Ointment (pink tube).
- lie down in bed. Insert applicator into vagina and inject Femiclear. Remain lying down to avoid leakage.
- discard applicator after use. DO NOT reuse.
- repeat on second night.

Itch Relief: squeeze ointment onto fingertips. Apply onto itchy, irritated skin outside the vagina (vulva) as needed.

- Children under 12 years: ask a doctor

Other information

- do not use if applicator wrapper is torn, open, or incompletely sealed
- do not use if seal over tube opening has been punctured
- do not purchase if carton is open
- Store at 68-77°F (20-25°C). If liquified, refrigerate 10 minutes to thicken.
- this a 2-dose treatment. Most women do not get complete relief of their symptoms in just 2 days. Most women get some improvement in 2 days and complete relief by 7 days.

Inactive ingredients

Vaginal Ointment: beeswax, essential oil (natural fragrance), oxygenated olive oil

Itch Relief: beeswax, colloidal oatmeal, essential oil (natural fragrance), oxygenated olive oil

Questions?

Call 512-401-3572 or visit FemiClear.com

Organicare, LLC, Austin, TX 78744, USA

Made and Distributed by

OrganiCare®

Austin, TX 78744, USA

Claims based on clinical and/or in vitro laboratory (non-human/non-animal) studies, and traditional homeopathic practice (not accepted clinical medical evidence; not FDA evaluated). See FemiClear.com.